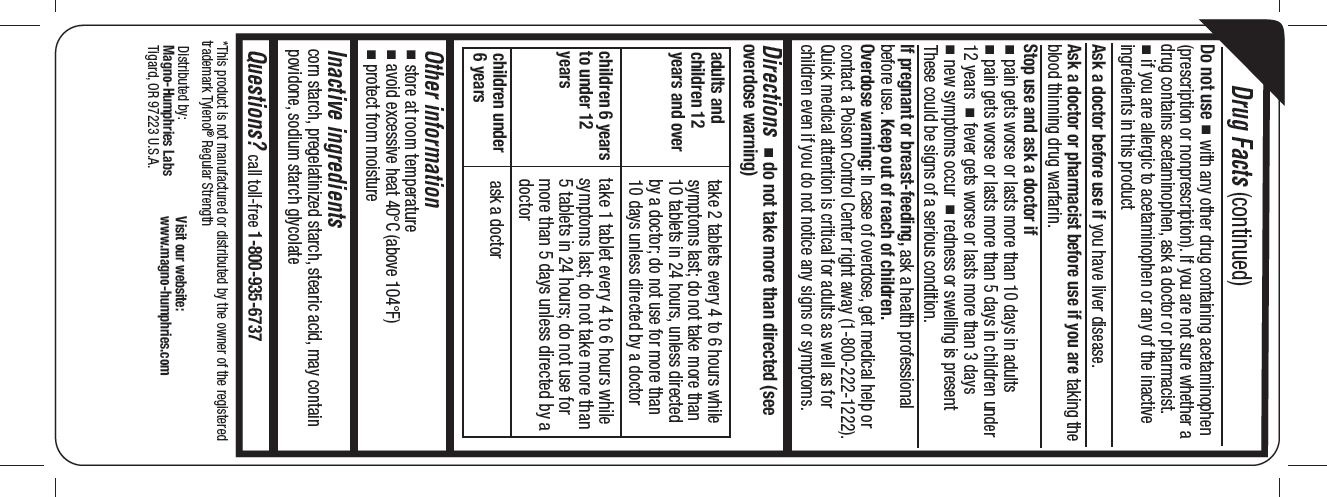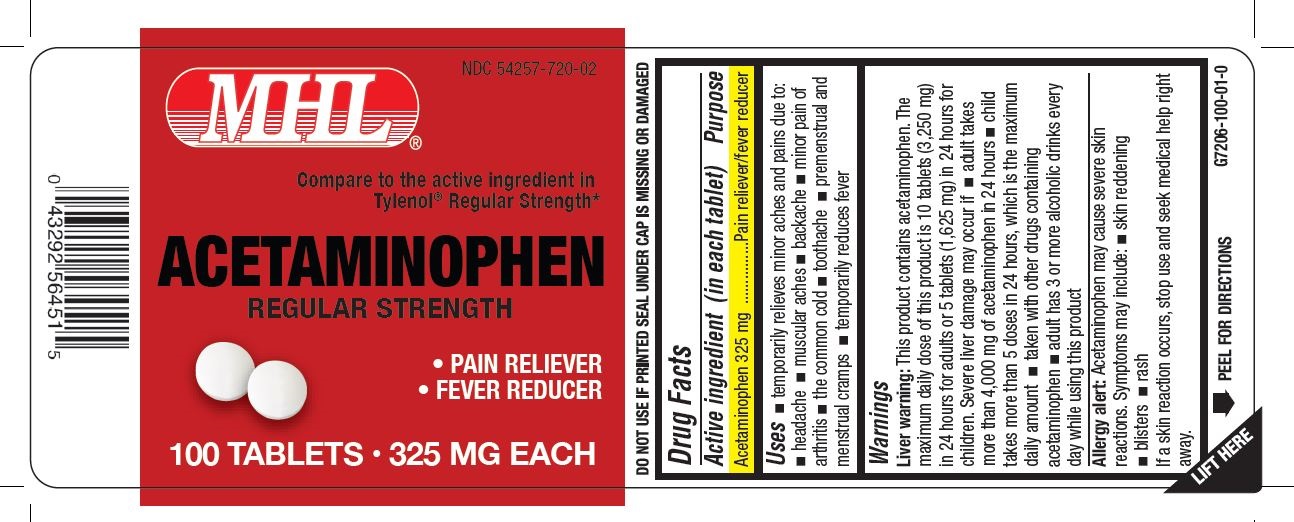 DRUG LABEL: Acetaminophen Regular Strength
NDC: 54257-720 | Form: TABLET
Manufacturer: Magno-Humphries, Inc.
Category: otc | Type: HUMAN OTC DRUG LABEL
Date: 20231027

ACTIVE INGREDIENTS: ACETAMINOPHEN 325 mg/1 1
INACTIVE INGREDIENTS: STARCH, CORN; STEARIC ACID

Acetaminophen Regular Strength

Active ingredient (in each caplet)

Acetaminophen 325 mg

Purpose

Pain reliever/fever reducer

Uses

- temporarily relieves minor aches and pains associated with:
- headache
- muscular aches
- backache
- arthritis
- common cold
- toothache
- menstrual cramps
- temporarily reduces fever

Warnings

This product contains acetaminophen. Severe liver damage may occur if you take Liver warning:

- more than 8 caplets in 24 hours, which is the maximum daily amount
- with other drugs containing acetaminophen
- 3 or more alcoholic drinks every day while using this product

Do not use

- with any other drugs containing acetaminophen (prescription or nonprescription). If you are not sure whether a drug contains acetaminophen, ask a doctor or pharmacist.
- if you are allergic to acetaminophen or any of the inactive ingredients in this product

Ask a doctor before use if you have

liver disease

Ask a doctor or pharmacist before use if you are

taking the blood thinning drug warfarin

Stop use and ask a doctor if

- new symptoms occur
- redness or swelling is present
- pain gets worse or lasts more than 10 days
- fever gets worse or lasts more than 3 days. These could be signs of a serious condition.

If pregnant or breast-feeding,

ask a health professional before use.

Keep out of reach of children.

Overdose warning: Taking more than the recommended dose (overdose) may cause liver damage. In case of overdose, get medical help or contact a Poison Control Center right away. Quick medical attention is critical for adults as well as for children even if you do not notice any signs or symptoms.

Directions

do not take more than directed (see overdose warning)

adults and children 12 years and over | - take 2 tablets every 4 to 6 hours as needed - do not take more than 8 tablets in 24 hours - do not take for more than 10 days unless directed by a doctor
children 6-11 years | - take 1 tablets every 4 to 6 hours as needed - do not take more than 4 tablets in 24 hours - do not take for more than 5 days unless directed by a doctor
children under 6 years | do not use this adult Regular Strength product in children under 6 years of age; this will provide more than the recommended dose (overdose) of acetaminophen and may cause liver damage.

Other information

- store at room temperature. Protect from moisture.
- avoid excessive heat 40ºC (above 104º F)

Inactive ingredients

Corn starch, pregelatinized starch, stearic acid, may contain povidone, sodium starch glycolate

Questions?

call toll-free 1-800-935-6737